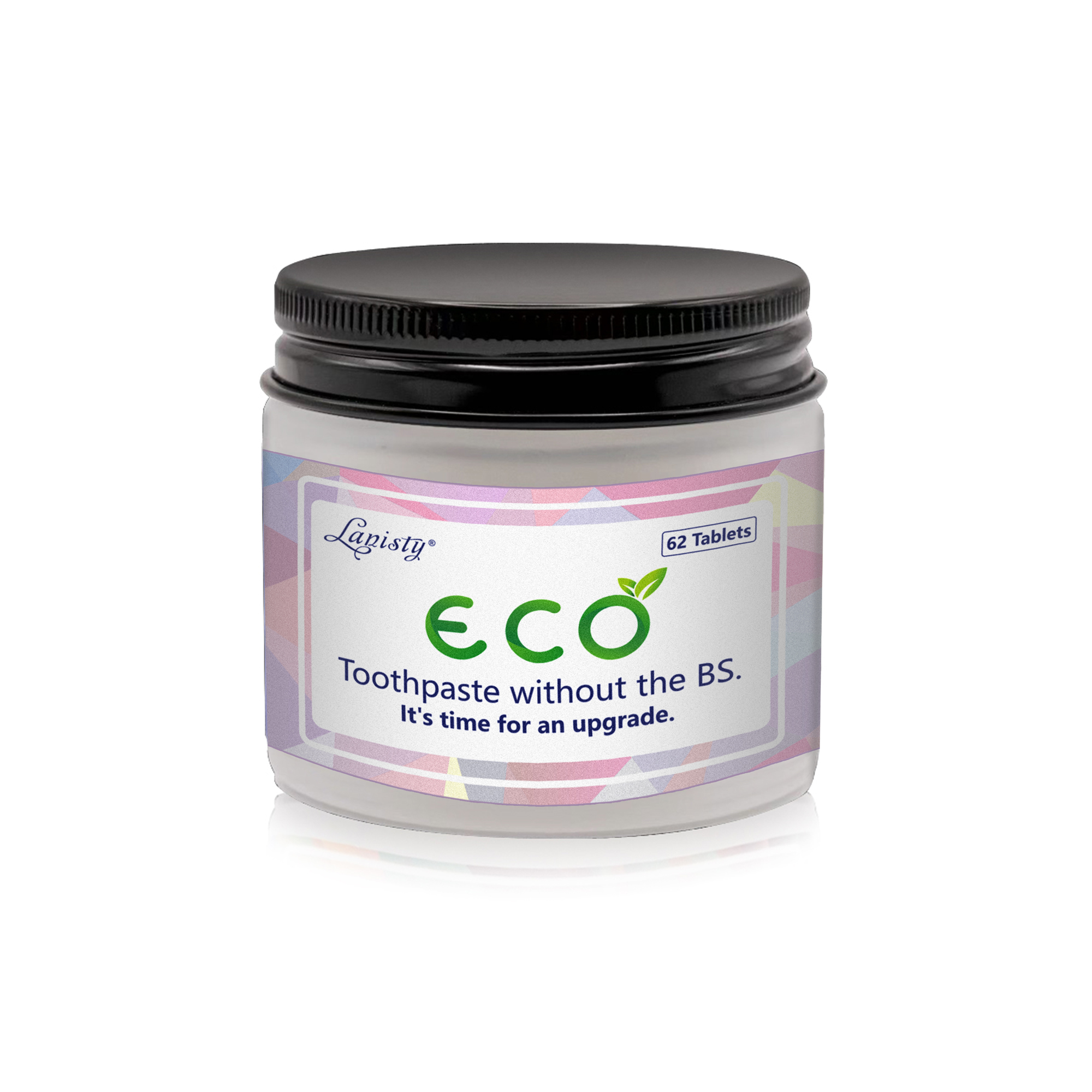 DRUG LABEL: Lanisty ToothpasteTablets
NDC: 84766-0001 | Form: TABLET
Manufacturer: COMFMET LIMITED
Category: otc | Type: HUMAN OTC DRUG LABEL
Date: 20241006

ACTIVE INGREDIENTS: SODIUM BICARBONATE 22 g/100 g; MENTHOL 9 g/100 g; LACTOBACILLUS ACIDOPHILUS 1 g/100 g
INACTIVE INGREDIENTS: SODIUM CHLORIDE 1 g/100 g; CALCIUM CARBONATE 13 g/100 g; XANTHAN GUM 3 g/100 g; EPIRUBICIN HYDROCHLORIDE 17 g/100 g; DIHYDROXYALUMINUM SODIUM CARBONATE 15 g/100 g; VANILLA 10 g/100 g; MALTODEXTRIN 17 g/100 g; SUCRALOSE 2 g/100 g; SODIUM LAURYL SULFATE 6 g/100 g; COCONUT SHELL 1 g/100 g

ACTIVE INGREDIENT

Sodium Bicarbonate - (Baking Soda) 22%
Menthol Formylethylamine - (Menthol) 9%
Lactobacillus - (Lactobacillus) 1%

Purpose

Keeps teeth white and strong.Keeps your mouth clean.Refreshes your mouth.Prevents tooth decay and elimina-tes bad breath.Enhances the aesthetic effectPrevention of gingivitis,periodontitis (pyorrhea alveolaris)Prevention of periodontal diseasePrevention of gum diseaseRemoval of plaque (Anti-plaque)

Uses

Keeps teeth white and strong

Warnings

Children need to be accompanied by a guadian

Do not use

if this toothpaste causes anydamage to the gums or mouth,discontinue use and consultyour doctor or dentist.

When Using

Avoid direct ingestion

Stop Use

if this toothpaste causes anydamage to the gums or mouth,discontinue use and consultyour doctor or dentist.

Ask Doctor

if a child under 6 years of ageswallows a large amount, imme-diately consult your doctor ordentist.

Keep Out Of Reach Of Children

if swallowed, get medical help orcontact Poison Control Center right away.

INDICATIONS AND USAGE

1.Grab up a tablet and plance it your mouth
2.Chew your tablet until fully dissolvrf.
3.Brush with a wet toothbrushfor two minutes twice a day

INACTIVE INGREDIENT

Maltodextrin
Sodium Carbonate
Light Calcium Carbonate
Essence
Sodium Lauryl Sulfate
Xanthan Gum
Trichlorogalactose
Bioactive Glass
Cocos Nucifera Shell Powder

Questions

Email: commet515@gmail.com

DOSAGE AND ADMINISTRATION

Place tablets in your mouth.
Chew until it foams.
Brush your teeth as usual. Use twice daily.